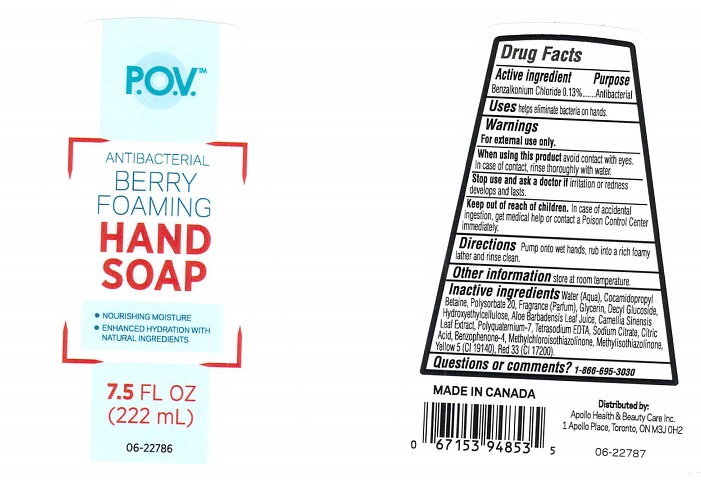 DRUG LABEL: P.O.V. Antibacterial Foaming Hand
NDC: 63148-197 | Form: SOAP
Manufacturer: Apollo Health and Beauty Care Inc.
Category: otc | Type: HUMAN OTC DRUG LABEL
Date: 20171113

ACTIVE INGREDIENTS: BENZALKONIUM CHLORIDE 1.3 mg/1 mL
INACTIVE INGREDIENTS: WATER; COCAMIDOPROPYL BETAINE; POLYSORBATE 20; GLYCERIN; DECYL GLUCOSIDE; HYDROXYETHYL CELLULOSE (5000 CPS AT 1%); ALOE VERA LEAF; GREEN TEA LEAF; POLYQUATERNIUM-7 (70/30 ACRYLAMIDE/DADMAC; 1600000 MW); EDETATE SODIUM; SODIUM CITRATE; CITRIC ACID MONOHYDRATE; SULISOBENZONE; METHYLCHLOROISOTHIAZOLINONE; METHYLISOTHIAZOLINONE; FD&C YELLOW NO. 5; D&C RED NO. 33

Drug Facts

Active ingredient

Benzalkonium Chloride 0.13%

Purpose

Antibacterial

Uses

helps eliminate bacteria on hands.

Warnings

For external use only.

When using this product

avoid contact with eyes. In case of contact, rinse thoroughly with water.

Stop use and ask a doctor if

irritation or redness develops and lasts.

Keep out of reach of children.

In case of accidental ingestion, get medical help or contact a Poison Control Center immediately.

Directions

Pump onto wet hands, rub into a rich foamy lather and rinse clean.

Other information

store at room temperature.

Inactive ingredients

Water (Aqua), Cocamidopropyl Betaine, Polysorbate 20, Fragrance (Parfum), Glyceirn, Decyl Glucoside, Hydroxyethylcellulose, Aloe Barbadensis Leaf Juice, Camellia Sinensis Leaf Extract, Polyquaternium-7, Tetrasodium EDTA, Sodium Citrate, Citric Acid, Benzophenone-4, Methylchloroisothiazolinone, Methylisothiazolinone, Yellow 5 (CI 19140), Red 33 (CI 17200).